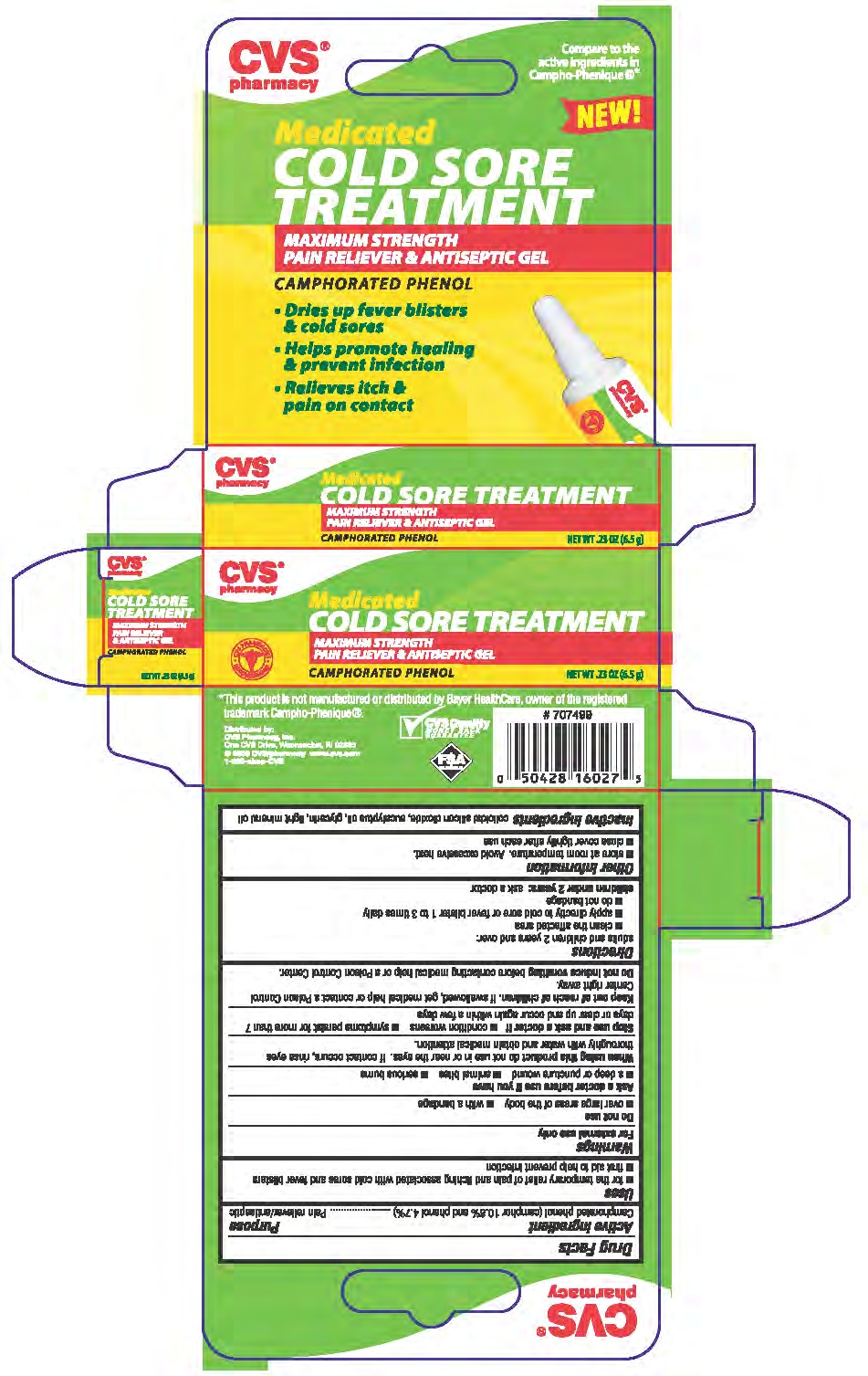 DRUG LABEL: CAMPHOR (SYNTHETIC) and PHENOL
NDC: 59779-088 | Form: GEL
Manufacturer: CVS
Category: otc | Type: HUMAN OTC DRUG LABEL
Date: 20110216

ACTIVE INGREDIENTS: CAMPHOR (SYNTHETIC) 108 mg/1 g; PHENOL 47 mg/1 g
INACTIVE INGREDIENTS: MINERAL OIL; EUCALYPTUS OIL; GLYCERIN ; SILICON DIOXIDE

drug facts

Active ingredient Purpose
Camphorated phenol (camphor 10.8% and phenoll 4.7%) .........................Pain reliever/antiseptic

Active ingredient Purpose
Camphorated phenol (camphor 10.8% and phenoll 4.7%) .........................Pain reliever/antiseptic
Use
- for the temporary relief of pain and itching associated with cold sores and fever blisters
- first aid to help prevent infection

KEEP OUT OF REACH OF CHILDREN

Keep out of the reach of children. If swallowed, get medical help or contact a Poison Control
Center right away.
Do not induce vomiting before contacting medical help or a Poison Control Center.

Uses
- for the temporary relief of pain and itching associated with cold sores and fever blisters
- first aid to help prevent infection

Warnings
For external use only.
______________________________________________________________________________
Do not use
- over large areas of the body - with a bandage
______________________________________________________________________________
Ask a doctor before use if you have
- a deep puncture wound - animal bites - serious burns
______________________________________________________________________________
When using this product do not use in or near the eyes. If contact occurs rinse eyes
thoroughly with water and obtain medical attention.
______________________________________________________________________________
Stop use and ask a doctor if - condition worsens -symptoms persist for more than 7
days or clear up and occur again within a few days
______________________________________________________________________________
Keep out of reach of children. If swallowed get medical help or contact a Poison Control
Center right away.
Do not induce vomiting before contacting medical help or a Poison Control Center

Directions
- adults and children two years and over:
- clean the affected area
- apply directly to teh cold sore or fever blister 1 to 3 times daily
- Do not bandage
Children under two years: ask a doctor
Other information
Store at room temperature. Avoid excessive heat.
Close cover tightly after each use

INACTIVE INGREDIENT

Inactive Ingredients colloided silicon dioxide, eucalyptus oil, glycerin, light mineral oil